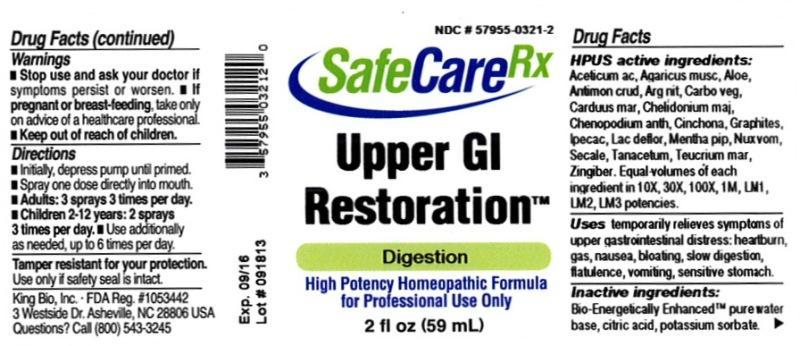 DRUG LABEL: Upper GI Restoration
NDC: 57955-0321 | Form: LIQUID
Manufacturer: King Bio Inc.
Category: homeopathic | Type: HUMAN OTC DRUG LABEL
Date: 20131022

ACTIVE INGREDIENTS: ACETIC ACID 10 [hp_X]/59 mL; AMANITA MUSCARIA FRUITING BODY 10 [hp_X]/59 mL; ALOE 10 [hp_X]/59 mL; ANTIMONY TRISULFIDE 10 [hp_X]/59 mL; SILVER NITRATE 10 [hp_X]/59 mL; ACTIVATED CHARCOAL 10 [hp_X]/59 mL; SILYBUM MARIANUM SEED 10 [hp_X]/59 mL; CHELIDONIUM MAJUS 10 [hp_X]/59 mL; DYSPHANIA AMBROSIOIDES 10 [hp_X]/59 mL; CINCHONA OFFICINALIS BARK 10 [hp_X]/59 mL; GRAPHITE 10 [hp_X]/59 mL; IPECAC 10 [hp_X]/59 mL; SKIM MILK 10 [hp_X]/59 mL; MENTHA PIPERITA 10 [hp_X]/59 mL; STRYCHNOS NUX-VOMICA SEED 10 [hp_X]/59 mL; CLAVICEPS PURPUREA SCLEROTIUM 10 [hp_X]/59 mL; TANACETUM VULGARE TOP 10 [hp_X]/59 mL; TEUCRIUM MARUM 10 [hp_X]/59 mL; GINGER 10 [hp_X]/59 mL
INACTIVE INGREDIENTS: WATER; CITRIC ACID MONOHYDRATE; POTASSIUM SORBATE

Upper GI Restoration™

Drug Facts

___________________________________________________________________________________________________________________

HPUS active ingredients: Aceticum acidum, Agaricus muscarius, Aloe socotrina, Antimonium crudum, Argentum nitricum, Carbo vegetabilis, Carduus marianus, Chelidonium majus, Chenopodium anthelminticum, Cinchona officinalis, Graphites, Ipecacuanha, Lac defloratum, Mentha piperita, Nux vomica, Secale cornutum, Tanacetum vulgare, Teucrium marum, Zingiber officinale. Equal volumes of each ingredient in 10X, 30X, 100X, 1M, LM1, LM2, LM3 potencies.

INDICATIONS AND USAGE

Uses temporarily relieves symptoms of upper gastrointestinal distress: heartburn, gas, nausea, bloating, slow digestion, flatulence, vomiting, sensitive stomach.

INACTIVE INGREDIENT

Inactive ingredients: Bio-Energetically Enhanced™ pure water base, citric acid, potassium sorbate.

Warnings

- Stop use and ask your doctor if symptoms persist or worsen.
- If pregnant or breast-feeding, take only on advice of a healthcare professional.

- Keep out of reach of children.

Directions

- Initially, depress pump until primed.
- Spray one dose directly into mouth.
- Adults: 3 sprays 3 times per day.
- Children 2-12 years: 2 sprays 3 times per day.
- Use additionally as needed, up to 6 times per day.

OTHER SAFETY INFORMATION

Tamper resistant for your protection. Use only if safety seal is intact.

PURPOSE

Uses temporarily relieves symptoms of upper gastrointestinal distress:

- heartburn
- gas
- nausea
- bloating
- slow digestion
- flatulence
- vomiting
- sensitive stomach